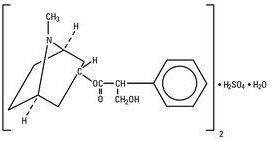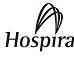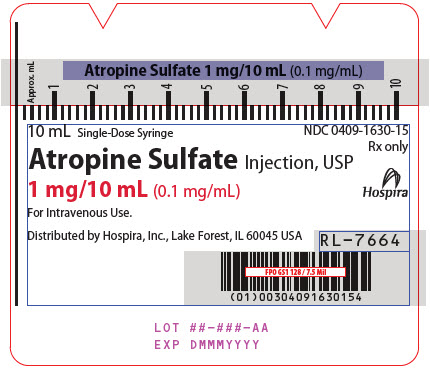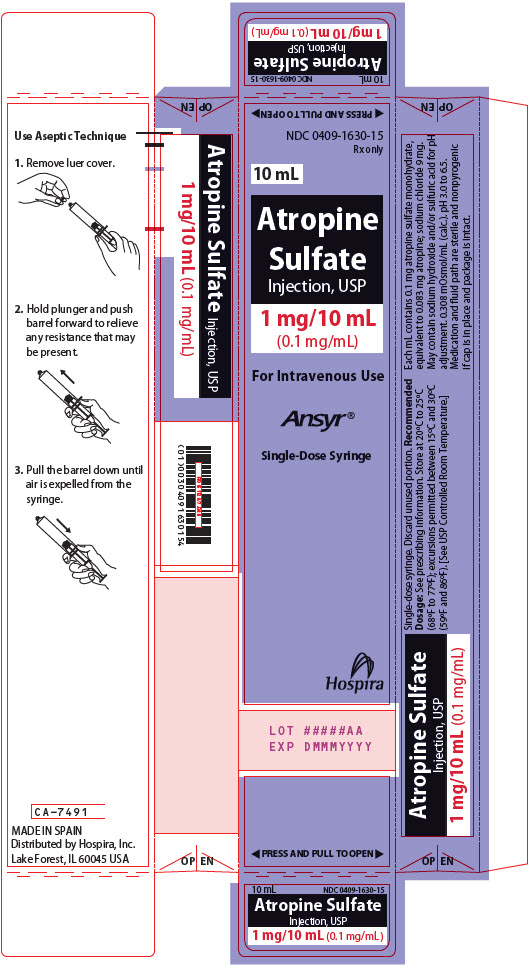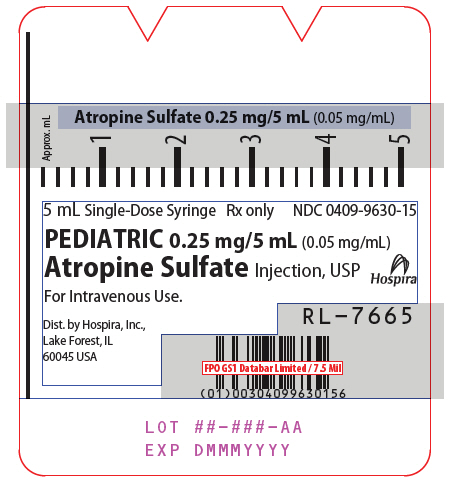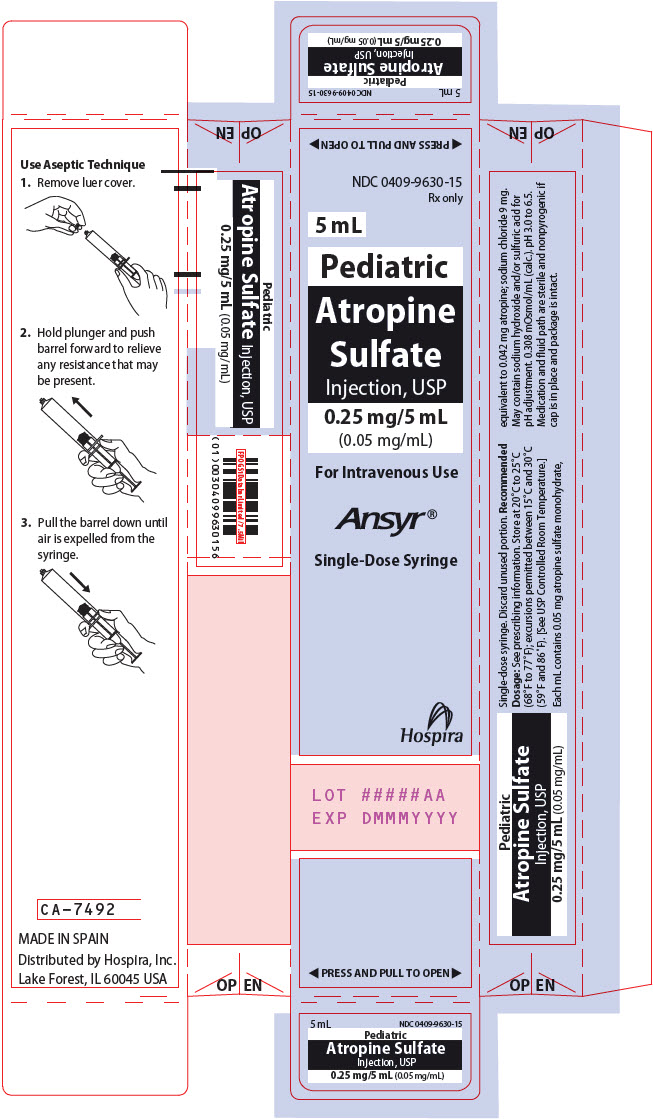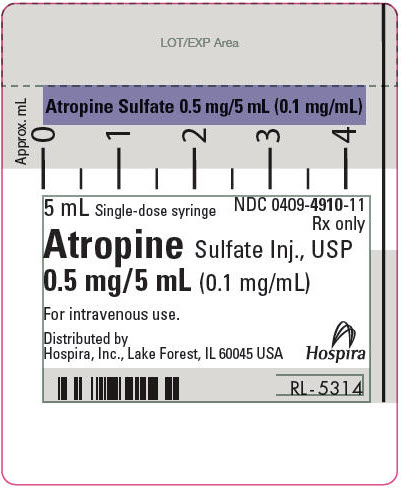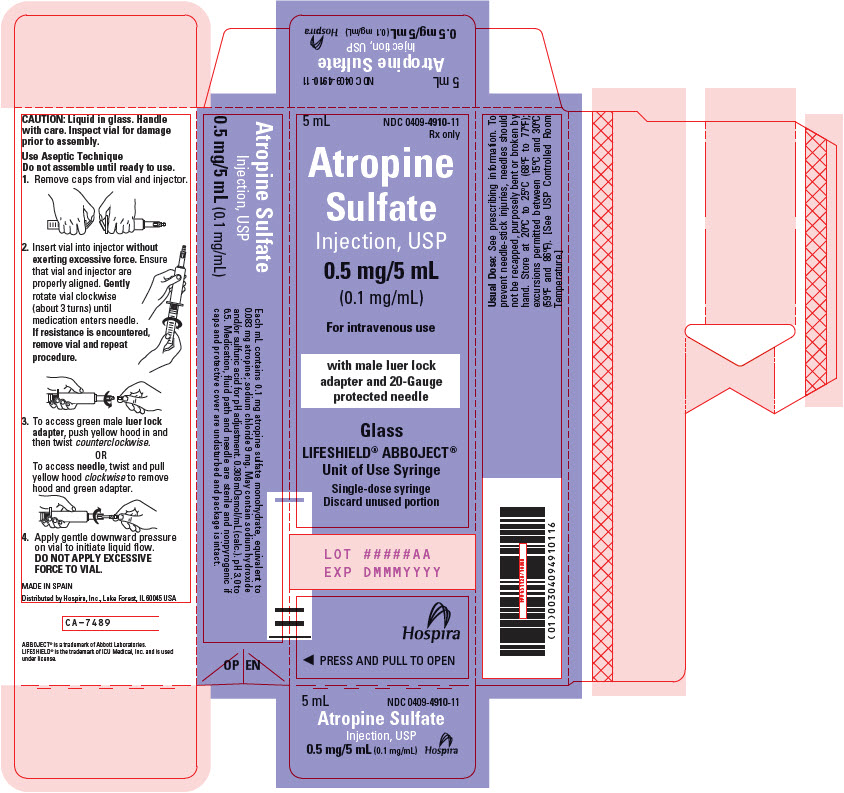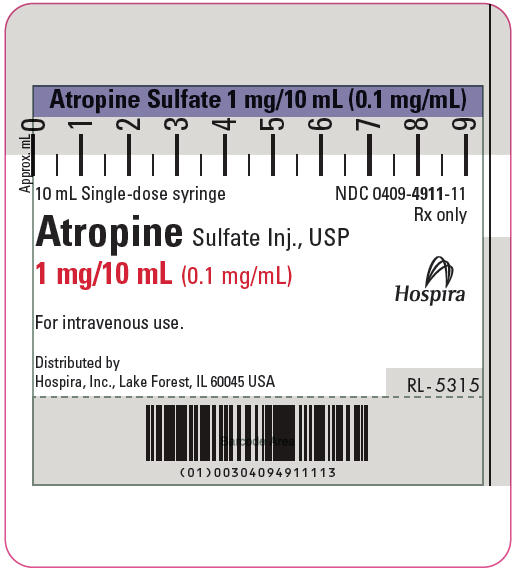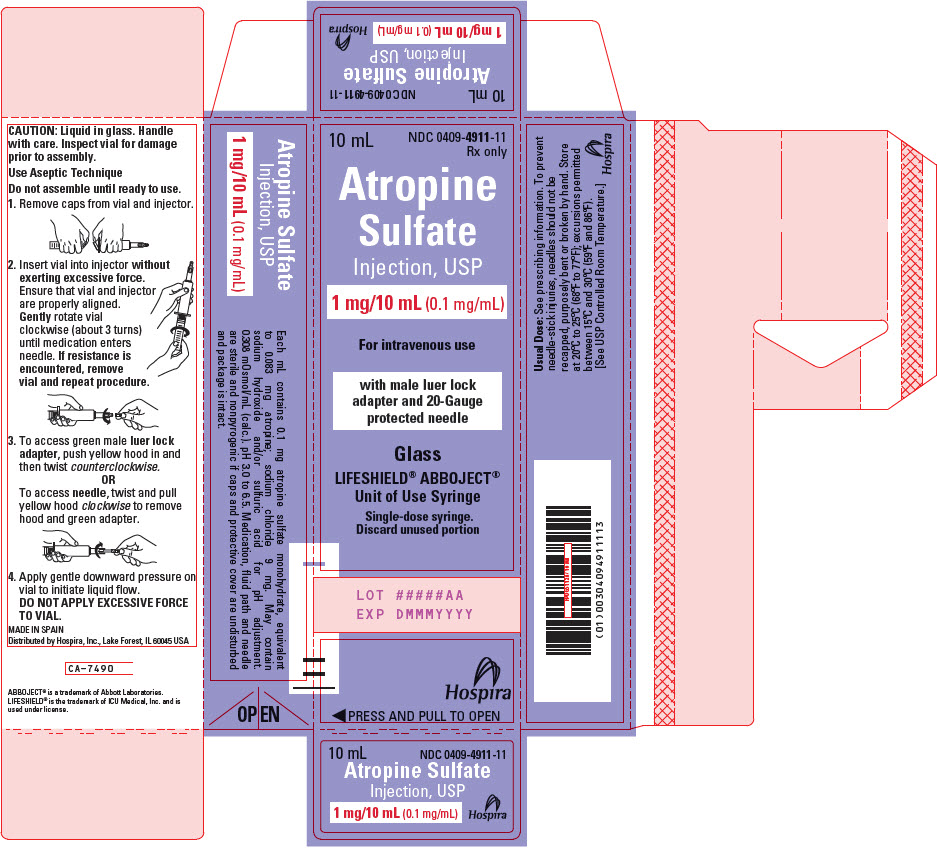 DRUG LABEL: Atropine Sulfate
NDC: 0409-1630 | Form: INJECTION, SOLUTION
Manufacturer: Hospira, Inc.
Category: prescription | Type: HUMAN PRESCRIPTION DRUG LABEL
Date: 20251112

ACTIVE INGREDIENTS: ATROPINE SULFATE 0.1 mg/1 mL
INACTIVE INGREDIENTS: SODIUM CHLORIDE 9 mg/1 mL; SODIUM HYDROXIDE; SULFURIC ACID; WATER

HIGHLIGHTS OF PRESCRIBING INFORMATION

These highlights do not include all the information needed to use ATROPINE SULFATE INJECTION safely and effectively. See full prescribing information for ATROPINE SULFATE INJECTION.
ATROPINE SULFATE injection, for intravenous use
Initial U.S. Approval: 1960

1 INDICATIONS AND USAGE

Atropine is a muscarinic antagonist indicated for temporary blockade of severe or life‑threatening muscarinic effects. (1)

2 DOSAGE AND ADMINISTRATION

- For intravenous administration (2.1)
- Titrate according to heart rate, PR interval, blood pressure and symptoms (2.1)
- Adult dosage
  - Antisialagogue or for antivagal effects: Initial single dose of 0.5 mg to 1 mg (2.2)
  - Antidote for organophosphorus or muscarinic mushroom poisoning: Initial single dose of 2 mg to 3 mg, repeated every 20-30 minutes (2.2)
  - Bradyasystolic cardiac arrest: 1 mg dose, repeated every 3-5 minutes if asystole persists (2.2)
- Patients with Coronary Artery Disease: Limit the total dose to 0.03 mg/kg to 0.04 mg/kg (2.4)

3 DOSAGE FORMS AND STRENGTHS

- 0.05 mg/mL injection in Ansyr® Plastic Syringe (3)
- 0.1 mg/mL injection in Ansyr® Plastic Syringe (3)
- 0.1 mg/mL injection in LifeShield® Abboject® Glass Syringe (3)

4 CONTRAINDICATIONS

None. (4)

5 WARNINGS AND PRECAUTIONS

- Tachycardia (5.1)
- Glaucoma (5.2)
- Pyloric obstruction (5.3)
- Worsening urinary retention (5.4)
- Viscid bronchial plugs (5.5)

6 ADVERSE REACTIONS

Most adverse reactions are directly related to atropine’s antimuscarinic action. Dryness of the mouth, blurred vision, photophobia and tachycardia commonly occur with chronic administration of therapeutic doses. (6)
To report SUSPECTED ADVERSE REACTIONS, contact Pfizer Inc. at 1-800-438-1985 or FDA at 1-800-FDA-1088 or www.fda.gov/medwatch.

7 DRUG INTERACTIONS

Mexiletine: Decreases rate of mexiletine absorption. (7.1)

FULL PRESCRIBING INFORMATION

1 INDICATIONS AND USAGE

Atropine Sulfate Injection is indicated for temporary blockade of severe or life‑threatening muscarinic effects, e.g., as an antisialagogue, an antivagal agent, an antidote for organophosphorus or muscarinic mushroom poisoning, and to treat bradyasystolic cardiac arrest.

2 DOSAGE AND ADMINISTRATION

2.1 General Administration

Parenteral drug products should be inspected visually for particulate matter and discoloration prior to administration, whenever solution and container permit. Do not administer unless solution is clear and seal is intact. Each syringe is intended for single dose only. Discard unused portion.

For intravenous administration.

Titrate based on heart rate, PR interval, blood pressure and symptoms.

2.2 Adult Dosage

Table 1: Recommended Dosage
Use | Dose (adults) | Repeat
Antisialagogue or other antivagal | 0.5 to 1 mg | 1-2 hours
Organophosphorus or muscarinic mushroom poisoning | 2 to 3 mg | 20-30 minutes
Bradyasystolic cardiac arrest | 1 mg | 3-5 minutes; 3 mg maximum total dose

2.3 Pediatric Dosage

Dosing in pediatric populations has not been well studied. Usual initial dose is 0.01 to 0.03 mg/kg.

2.4 Dosing in Patients with Coronary Artery Disease

Limit the total dose of atropine sulfate to 0.03 mg/kg to 0.04 mg/kg [see Warnings and Precautions (5.1)].

3 DOSAGE FORMS AND STRENGTHS

Injection: 0.05 mg/mL and 0.1 mg/mL in Ansyr® Plastic Syringe.

Injection: 0.1 mg/mL in LifeShield® Abboject® Glass Syringe.

4 CONTRAINDICATIONS

None.

5 WARNINGS AND PRECAUTIONS

5.1 Tachycardia

When the recurrent use of atropine is essential in patients with coronary artery disease, the total dose should be restricted to 2 to 3 mg (maximum 0.03 to 0.04 mg/kg) to avoid the detrimental effects of atropine‑induced tachycardia on myocardial oxygen demand.

5.2 Acute Glaucoma

Atropine may precipitate acute glaucoma.

5.3 Pyloric Obstruction

Atropine may convert partial organic pyloric stenosis into complete obstruction.

5.4 Complete Urinary Retention

Atropine may lead to complete urinary retention in patients with prostatic hypertrophy.

5.5 Viscid Plugs

Atropine may cause inspissation of bronchial secretions and formation of viscid plugs in patients with chronic lung disease.

6 ADVERSE REACTIONS

The following adverse reactions have been identified during post-approval use of atropine sulfate. Because these reactions are reported voluntarily from a population of uncertain size, it is not always possible to reliably estimate their frequency or establish a causal relationship to drug exposure.

Most of the side effects of atropine are directly related to its antimuscarinic action. Dryness of the mouth, blurred vision, photophobia and tachycardia commonly occur. Anhidrosis can produce heat intolerance. Constipation and difficulty in micturition may occur in elderly patients. Occasional hypersensitivity reactions have been observed, especially skin rashes which in some instances progressed to exfoliation.

7 DRUG INTERACTIONS

7.1 Mexiletine

Atropine Sulfate Injection decreased the rate of mexiletine absorption without altering the relative oral bioavailability; this delay in mexiletine absorption was reversed by the combination of atropine and intravenous metoclopramide during pretreatment for anesthesia.

8 USE IN SPECIFIC POPULATIONS

8.1 Pregnancy

Risk Summary

There are risks to the mother and fetus associated with untreated severe or life-threatening muscarinic events (see Clinical Considerations). Available data from published observational studies on atropine sulfate use in pregnant women are insufficient to evaluate for a drug‑associated risk of major birth defects, miscarriage, or adverse maternal or fetal outcomes (see Data). Animal developmental and reproductive toxicity studies have not been conducted with atropine.

Clinical Considerations

Disease-Associated Maternal and/or Embryo/Fetal Risk

Severe or life-threatening muscarinic events such as acute organophosphate poisoning and symptomatic bradycardia are medical emergencies in pregnancy which can be fatal if left untreated. Life-sustaining therapy for the pregnant woman should not be withheld because of concerns regarding the effects of atropine on the fetus.

Data

Human Data

Atropine crosses the placenta [see Clinical Pharmacology (12.3)]. No adequate and well-controlled studies are available regarding use of atropine in pregnant women.

In a cohort study of 401 pregnancies in the first trimester and 797 pregnancies in the second or third trimester, atropine use was not associated with an increased risk of congenital malformations. In a surveillance study, 381 newborns were exposed to atropine during the first trimester; 18 major birth defects were observed when 16 were expected. No specific pattern of major defects was identified. In another surveillance study of 50 pregnancies in the first trimester, atropine use was not associated with an increased risk of malformations. Methodological limitations of these observational studies including the inability to control for the dosage and timing of atropine exposure, underlying maternal disease, or concomitant maternal drug use, cannot definitively establish or exclude any drug-associated risk during pregnancy.

8.2 Lactation

Risk Summary

Trace amounts of atropine have been reported in human milk. There are no available data on atropine levels in human milk after intravenous injection, the effects on the breastfed infant, or the effects on milk production.

Clinical Considerations

Minimizing Exposure

The elimination half-life of atropine is more than doubled in children less than 2 years of age [see Clinical Pharmacology (12.3)]. To minimize potential infant exposure to Atropine Sulfate Injection, a woman may pump and discard her milk for 24 hours after use before resuming to breastfeed her infant.

8.4 Pediatric Use

Recommendations for use in pediatric patients are not based on clinical trials.

8.5 Geriatric Use

An evaluation of current literature revealed no clinical experience identifying differences in response between elderly and younger patients. In general, dose selection for an elderly patient should be cautious, usually starting at the low end of the dosing range, reflecting the greater frequency of decreased hepatic, renal, or cardiac function, and of concomitant disease or other drug therapy.

10 OVERDOSAGE

Excessive dosing may cause palpitation, dilated pupils, difficulty in swallowing, hot dry skin, thirst, dizziness, restlessness, tremor, fatigue and ataxia. Toxic doses lead to restlessness and excitement, hallucinations, delirium and coma. Depression and circulatory collapse occur only with severe intoxication. In such cases, blood pressure declines and death due to respiratory failure may ensue following paralysis and coma.

The fatal adult dose of atropine is not known. In pediatric populations, 10 mg or less may be fatal.

In the event of toxic overdosage, a short acting barbiturate or diazepam may be given as needed to control marked excitement and convulsions. Large doses for sedation should be avoided because central depressant action may coincide with the depression occurring late in atropine poisoning. Central stimulants are not recommended.

Physostigmine, given as an atropine antidote by slow intravenous injection of 1 to 4 mg (0.5 to 1 mg in pediatric populations), rapidly abolishes delirium and coma caused by large doses of atropine. Since physostigmine is rapidly destroyed, the patient may again lapse into coma after one to two hours, and repeated doses may be required.

Artificial respiration with oxygen may be necessary. Ice bags and alcohol sponges help to reduce fever, especially in pediatric populations.

Atropine is not removed by dialysis.

11 DESCRIPTION

Atropine Sulfate Injection, USP is a sterile, nonpyrogenic isotonic solution of atropine sulfate monohydrate in water for injection with sodium chloride sufficient to render the solution isotonic. It is administered parenterally by intravenous injection.

Each milliliter (mL) contains 0.1 mg (adult strength) or 0.05 mg (pediatric strength) of atropine sulfate monohydrate equivalent to 0.083 mg (adult strength) or 0.042 mg (pediatric strength) of atropine, and sodium chloride, 9 mg. May contain sodium hydroxide and/or sulfuric acid for pH adjustment 0.308 mOsmol/mL (calc.). pH 3.0 to 6.5.

Sodium chloride added to render the solution isotonic for injection of the active ingredient is present in amounts insufficient to affect serum electrolyte balance of sodium (Na^+) and chloride (Cl^-) ions.

The solution contains no bacteriostat, antimicrobial agent or added buffer (except for pH adjustment) and is intended for use only as a single-dose injection. When smaller doses are required the unused portion should be discarded.

Atropine Sulfate, USP is chemically designated 1α H, 5α H-Tropan-3-α-ol (±)-tropate (ester), sulfate (2:1) (salt) monohydrate, (C17H23NO3)2 H2SO4 H2O, colorless crystals or white crystalline powder very soluble in water. It has the following structural formula:

Atropine, a naturally occurring belladonna alkaloid, is a racemic mixture of equal parts of d- and 1‑hyocyamine, whose activity is due almost entirely to the levo isomer of the drug.

Sodium Chloride, USP is chemically designated NaCl, a white crystalline powder freely soluble in water.

The Ansyr® syringe is molded from a specially formulated polypropylene. Water permeates from inside the container at an extremely slow rate which will have an insignificant effect on solution concentration over the expected shelf life. Solutions in contact with the plastic container may leach out certain chemical components from the plastic in very small amounts; however, biological testing was supportive of the safety of the syringe material.

12 CLINICAL PHARMACOLOGY

12.1 Mechanism of Action

Atropine is an antimuscarinic agent since it antagonizes the muscarine-like actions of acetylcholine and other choline esters.

Atropine inhibits the muscarinic actions of acetylcholine on structures innervated by postganglionic cholinergic nerves, and on smooth muscles which respond to endogenous acetylcholine but are not so innervated. As with other antimuscarinic agents, the major action of atropine is a competitive or surmountable antagonism which can be overcome by increasing the concentration of acetylcholine at receptor sites of the effector organ (e.g., by using anticholinesterase agents which inhibit the enzymatic destruction of acetylcholine). The receptors antagonized by atropine are the peripheral structures that are stimulated or inhibited by muscarine (i.e., exocrine glands and smooth and cardiac muscle). Responses to postganglionic cholinergic nerve stimulation also may be inhibited by atropine but this occurs less readily than with responses to injected (exogenous) choline esters.

12.2 Pharmacodynamics

Atropine-induced parasympathetic inhibition may be preceded by a transient phase of stimulation, especially on the heart where small doses first slow the rate before characteristic tachycardia develops due to paralysis of vagal control. Atropine exerts a more potent and prolonged effect on heart, intestine and bronchial muscle than scopolamine, but its action on the iris, ciliary body and certain secretory glands is weaker than that of scopolamine. Unlike the latter, atropine in clinical doses does not depress the central nervous system but may stimulate the medulla and higher cerebral centers. Although mild vagal excitation occurs, the increased respiratory rate and (sometimes) increased depth of respiration produced by atropine are more probably the result of bronchiolar dilatation. Accordingly, atropine is an unreliable respiratory stimulant and large or repeated doses may depress respiration.

Adequate doses of atropine abolish various types of reflex vagal cardiac slowing or asystole. The drug also prevents or abolishes bradycardia or asystole produced by injection of choline esters, anticholinesterase agents or other parasympathomimetic drugs, and cardiac arrest produced by stimulation of the vagus. Atropine also may lessen the degree of partial heart block when vagal activity is an etiologic factor. In some patients with complete heart block, the idioventricular rate may be accelerated by atropine; in others, the rate is stabilized. Occasionally a large dose may cause atrioventricular (A-V) block and nodal rhythm.

Atropine Sulfate Injection in clinical doses counteracts the peripheral dilatation and abrupt decrease in blood pressure produced by choline esters. However, when given by itself, atropine does not exert a striking or uniform effect on blood vessels or blood pressure. Systemic doses slightly raise systolic and lower diastolic pressures and can produce significant postural hypotension. Such doses also slightly increase cardiac output and decrease central venous pressure. Occasionally, therapeutic doses dilate cutaneous blood vessels, particularly in the “blush” area (atropine flush) and may cause atropine “fever” due to suppression of sweat gland activity in infants and small children.

The effects of intravenous atropine on heart rate (maximum heart rate) and saliva flow (minimum flow) after intravenous administration (rapid, constant infusion over three minutes) are delayed by 7 to 8 minutes after drug administration and both effects are non-linearly related to the amount of drug in the peripheral compartment. Changes in plasma atropine levels following intramuscular administration (0.5 to 4 mg doses) and heart rate are closely overlapped but the time course of the changes in atropine levels and behavioral impairment indicates that pharmacokinetics is not the primary rate-limiting mechanism for the central nervous system effect of atropine.

12.3 Pharmacokinetics

Atropine disappears rapidly from the blood following injection and is distributed throughout the body. Exercise, both prior to and immediately following intramuscular administration of atropine, significantly increases the absorption of atropine due to increased perfusion in the muscle and significantly decreases the clearance of atropine. The pharmacokinetics of atropine is nonlinear after intravenous administration of 0.5 to 4 mg. Atropine’s plasma protein binding is about 44% and saturable in the 2‑20 μg/mL concentration range. Atropine readily crosses the placental barrier and enters the fetal circulation, but is not found in amniotic fluid. Much of the drug is destroyed by enzymatic hydrolysis, particularly in the liver; from 13 to 50% is excreted unchanged in the urine. Traces are found in various secretions, including milk. The major metabolites of atropine are noratropine, atropin-n-oxide, tropine, and tropic acid. The metabolism of atropine is inhibited by organophosphate pesticides.

Specific Populations

The elimination half-life of atropine is more than doubled in children under two years old and the elderly (>65 years old) compared to other age groups. There is no gender effect on the pharmacokinetics and pharmacodynamics (heart rate changes) of atropine.

13 NONCLINICAL TOXICOLOGY

13.1 Carcinogenesis, Mutagenesis, Impairment of Fertility

Studies have not been performed to evaluate the carcinogenic or mutagenic potential of atropine or its potential to affect fertility adversely.

16 HOW SUPPLIED/STORAGE AND HANDLING

Atropine Sulfate Injection, USP is supplied in single-dose syringes as follows:

Unit of Sale and Product Description | Strength; (Concentration) | NDC
Bundle of 10; 5 mL Single-Dose Ansyr® Plastic Syringe | 0.25 mg/5 mL; (0.05 mg/mL) | 0409-9630-05
Bundle of 10; 10 mL Single-Dose Ansyr® Plastic Syringe | 1 mg/10 mL; (0.1 mg/mL) | 0409-1630-10
Bundle of 10; 5 mL Single-Dose LifeShield® Abboject® Glass Syringe | 0.5 mg/5 mL; (0.1 mg/mL) | 0409-4910-34
Bundle of 10; 10 mL Single-Dose LifeShield® Abboject® Glass Syringe | 1 mg/10 mL; (0.1 mg/mL) | 0409-4911-34

Store at 20°C to 25°C (68°F to 77°F); excursions permitted between 15°C and 30°C (59°F and 86°F). [See USP Controlled Room Temperature.]

Distributed by Hospira, Inc., Lake Forest, IL 60045 USA

Abboject® is a trademark of Abbott Laboratories.

LifeShield® is the trademark of ICU Medical, Inc. and is used under license.

LAB-1041-7.0

PRINCIPAL DISPLAY PANEL - 10 mL Syringe Label

Atropine Sulfate 1 mg/10 mL (0.1 mg/mL)

10 mL Single-Dose Syringe

NDC 0409-1630-15
Rx only

Atropine Sulfate Injection, USP
1 mg/10 mL (0.1 mg/mL)

Hospira

For Intravenous Use.

Distributed by Hospira, Inc., Lake Forest, IL 60045 USA

RL-7664

LOT ##-###-AA
EXP DMMMYYYY

PRINCIPAL DISPLAY PANEL - 10 mL Syringe Carton

NDC 0409-1630-15
Rx only

10 mL

Atropine
Sulfate
Injection, USP

1 mg/10 mL
(0.1 mg/mL)

For Intravenous Use

Ansyr®

Single-Dose Syringe

Hospira

LOT #####AA
EXP DMMMYYYY

◀ PRESS AND PULL TO OPEN ▶

PRINCIPAL DISPLAY PANEL - 5 mL Syringe Label

Atropine Sulfate 0.25 mg/5 mL (0.05 mg/mL)

5 mL Single-Dose Syringe
Rx only
NDC 0409-9630-15

PEDIATRIC 0.25 mg/5 mL (0.05 mg/mL)
Atropine Sulfate Injection, USP

Hospira

For Intravenous Use.

Dist. by Hospira, Inc.,
Lake Forest, IL
60045 USA

RL-7665

LOT ##-###-AA
EXP DMMMYYYY

PRINCIPAL DISPLAY PANEL - 5 mL Syringe Carton

NDC 0409-9630-15
Rx only

5 mL

Pediatric
Atropine
Sulfate
Injection, USP

0.25 mg/5 mL
(0.05 mg/mL)

For Intravenous Use

Ansyr®

Single-Dose Syringe

Hospira

LOT #####AA
EXP DMMMYYYY

◀ PRESS AND PULL TO OPEN ▶

PRINCIPAL DISPLAY PANEL - 5 mL Syringe Label - 0409-4910

5 mL Single-dose syringe

NDC 0409-4910-11
Rx only

Atropine Sulfate Inj., USP
0.5 mg/5 mL (0.1 mg/mL)

For intravenous use.

Distributed by
Hospira, Inc., Lake Forest, IL 60045 USA

Hospira

RL-5314

PRINCIPAL DISPLAY PANEL - 5 mL Syringe Carton - 0409-4910

5 mL
NDC 0409-4910-11
Rx only

Atropine
Sulfate
Injection, USP
0.5 mg/5 mL
(0.1 mg/mL)

For intravenous use

with male luer lock
adapter and 20-Gauge
protected needle

Glass
LIFESHIELD® ABBOJECT®
Unit of Use Syringe

Single-dose syringe
Discard unused portion

LOT #####AA
EXP DMMMYYYY

Hospira

◀ PRESS AND PULL TO OPEN

PRINCIPAL DISPLAY PANEL - 10 mL Syringe Label - 0409-4911

10 mL Single-dose syringe

NDC 0409-4911-11
Rx only

Atropine Sulfate Inj., USP
1 mg/10 mL (0.1 mg/mL)

For intravenous use.

Distributed by
Hospira, Inc., Lake Forest, IL 60045 USA

Hospira

RL-5315

PRINCIPAL DISPLAY PANEL - 10 mL Syringe Carton - 0409-4911

10 mL
NDC 0409-4911-11
Rx only

Atropine
Sulfate
Injection, USP
1 mg/10 mL (0.1 mg/mL)

For intravenous use

with male luer lock
adapter and 20-Gauge
protected needle

Glass
LIFESHIELD® ABBOJECT®
Unit of Use Syringe

Single-dose syringe.
Discard unused portion

LOT #####AA
EXP DMMMYYYY

Hospira

◀ PRESS AND PULL TO OPEN